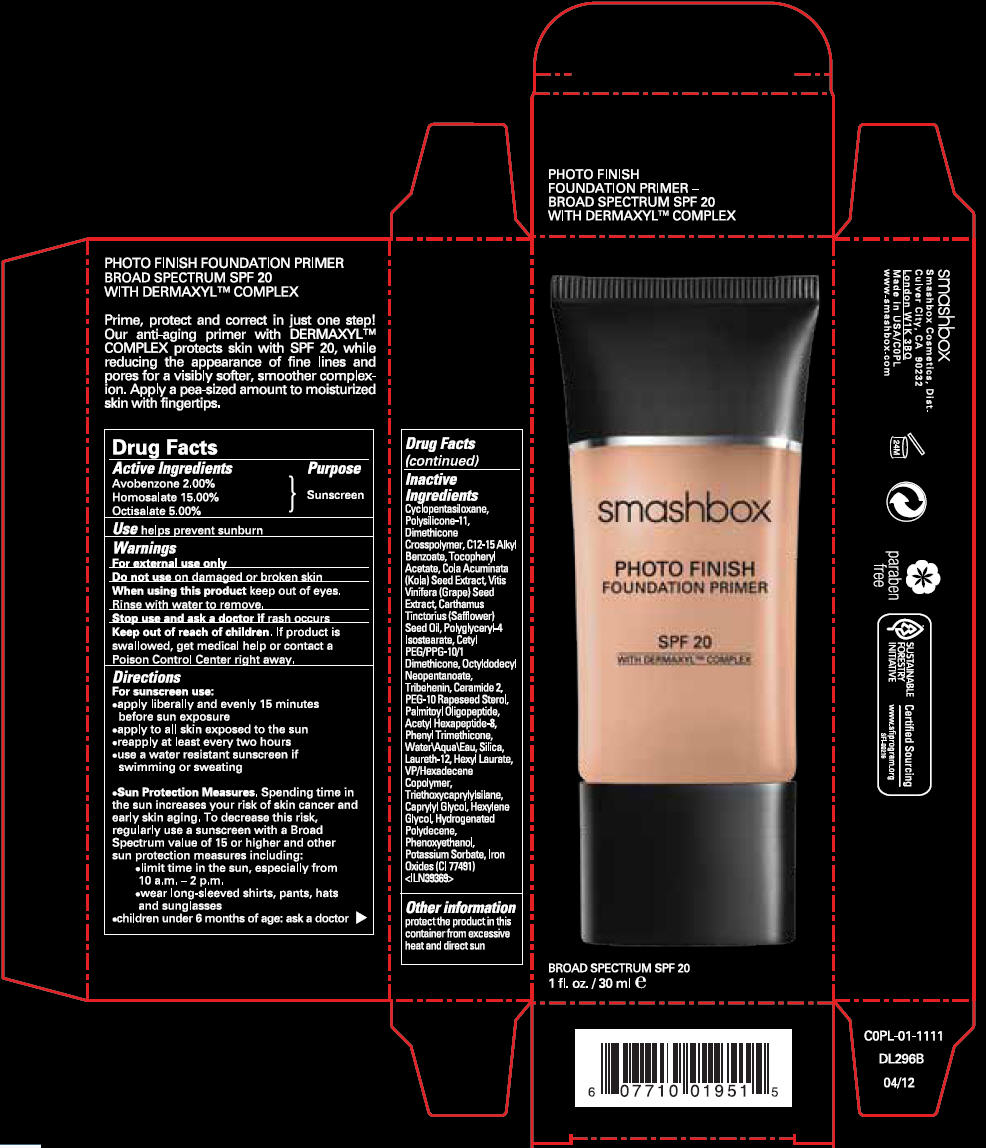 DRUG LABEL: PHOTO FINISH FOUNDATION PRIMER SPF 20
NDC: 59735-450 | Form: CREAM
Manufacturer: MANA PRODUCTS, INC.
Category: otc | Type: HUMAN OTC DRUG LABEL
Date: 20240103

ACTIVE INGREDIENTS: HOMOSALATE 15 g/100 g; OCTISALATE 5 g/100 g; AVOBENZONE 2 g/100 g
INACTIVE INGREDIENTS: ALKYL (C12-15) BENZOATE; VITIS VINIFERA SEED; SAFFLOWER OIL; POLYGLYCERYL-4 ISOSTEARATE; CERAMIDE NG; PEG-10 RAPESEED STEROL; ACETYL HEXAPEPTIDE-8; SILICON DIOXIDE; LAURETH-12; CAPRYLYL GLYCOL; HEXYLENE GLYCOL; FERRIC OXIDE RED; PALMITOYL HEXAPEPTIDE-12; PHENYL TRIMETHICONE; CYCLOMETHICONE 5; WATER; HEXYL LAURATE; TRIETHOXYCAPRYLYLSILANE; PHENOXYETHANOL; POTASSIUM SORBATE; .ALPHA.-TOCOPHEROL ACETATE; COLA ACUMINATA SEED; OCTYLDODECYL NEOPENTANOATE; TRIBEHENIN

PHOTO FINISH FND PRIMER SPF

ACTIVE INGREDIENTS

Avobenzone 2.00%
Homosalate 15.00%
Octisalate 5.00%

PURPOSE

Sunscreen

USES

helps prevent sunburn

WARNING

- For external use only
- Do not use on damaged or broken skin
- When using this product keep out of eyes. Rinse with water to remove.

DIRECTIONS

For sunscreen use:

- apply liberally and evenly 15 minutes before sun exposure
- apply to all skin exposed to the sun
- reapply at least every two hours
- use a water resistant sunscreen if swimming or sweating

Sun Protection Measures. Spending time in the sun increases your risk of skin cancer and early skin aging. To decrease this risk, regularly use a sunscreen with a Broad Spectrum value of 15 or higher and other sun protection measures including:

- limit time in the sun, especially from 10 a.m. – 2 p.m.
- wear long-sleeved shirts, pants, hats and sunglasses
- children under 6 months of age: ask a doctor

INACTIVE INGREDIENTS

Cyclopentasiloxane, Polysilicone-11, Dimethicone Crosspolymer, C12-15 Alkyl Benzoate, Tocopheryl Acetate, Cola Acuminata (Kola) Seed Extract, Vitis Vinifera (Grape) Seed Extract, Carthamus Tinctorius (Safflower) Seed Oil, Polyglyceryl-4 Isostearate, Cetyl PEG/PPG-10/1 Dimethicone, Octyldodecyl Neopentanoate, Tribehenin, Ceramide 2, PEG-10 Rapeseed Sterol, Palmitoyl Oligopeptide, Acetyl Hexapeptide-8, Phenyl Trimethicone, Water\Aqua\Eau, Silica, Laureth-12, Hexyl Laurate, VP/Hexadecene Copolymer, Triethoxycaprylylsilane, Caprylyl Glycol, Hexylene Glycol, Hydrogenated Polydecene, Phenoxyethanol, Potassium Sorbate, Iron Oxides (CI 77491) <ILN39369>

OTHER INFORMATION

protect the product in this container from excessive heat and direct sun

Stop use and ask a doctor if rash occurs.

RECENT MAJOR CHANGES

Dosage & Admin update

Keep out of reach of children. If product is swallowed, get medical help or contact a Poison Control Center right away.